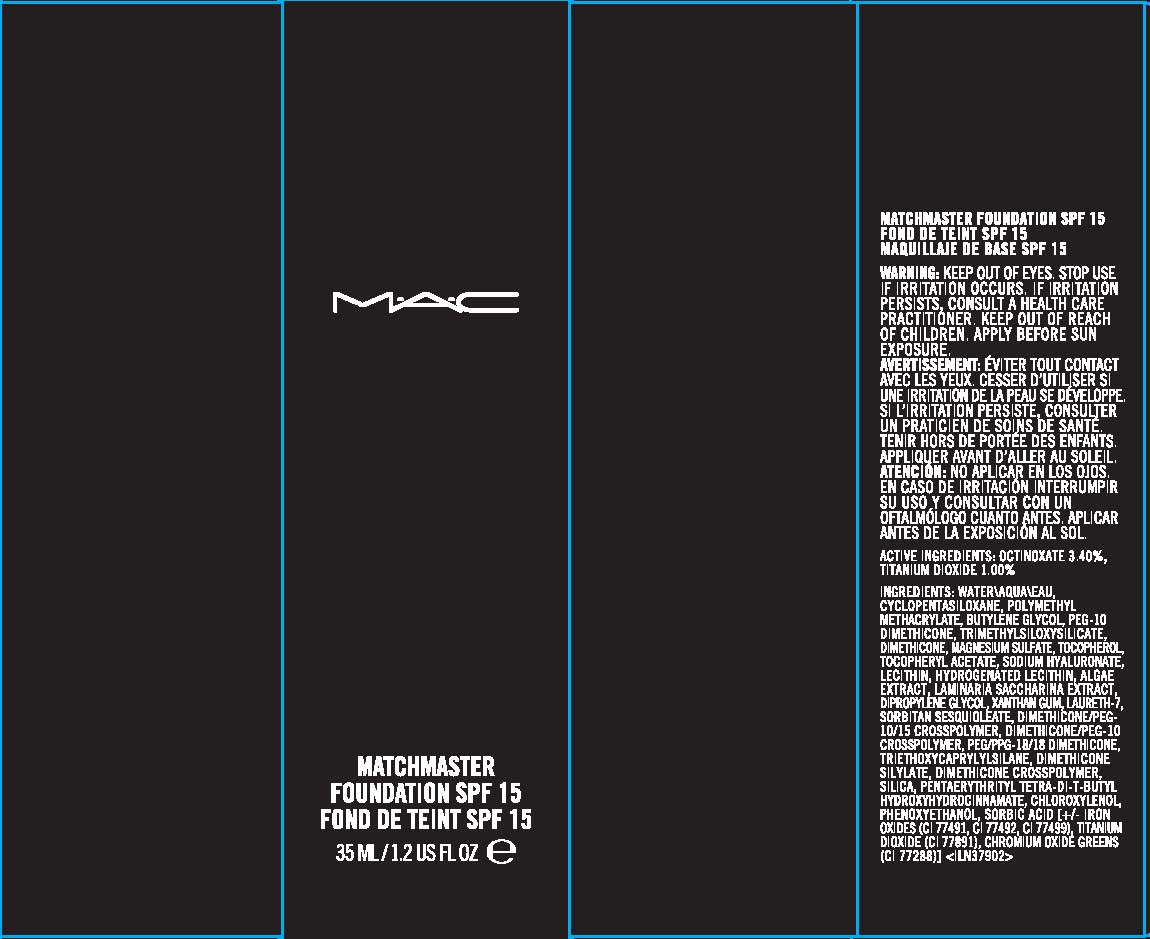 DRUG LABEL: MATCHMASTER FOUNDATION
NDC: 40046-0045 | Form: LOTION
Manufacturer: MAKEUP ART COSMETICS
Category: otc | Type: HUMAN OTC DRUG LABEL
Date: 20110712

ACTIVE INGREDIENTS: OCTINOXATE 3.4 mL/100 mL; TITANIUM DIOXIDE 1.0 mL/100 mL
INACTIVE INGREDIENTS: WATER; CYCLOMETHICONE 5; BUTYLENE GLYCOL; TRIMETHYLSILANE; DIMETHICONE; MAGNESIUM SULFATE, UNSPECIFIED; ALPHA-TOCOPHEROL; ALPHA-TOCOPHEROL ACETATE; HYALURONATE SODIUM; LECITHIN, SOYBEAN; HYDROGENATED SOYBEAN LECITHIN; SEAWEED; DIPROPYLENE GLYCOL; XANTHAN GUM; LAURETH-7; SORBITAN SESQUIOLEATE; TRIETHOXYCAPRYLYLSILANE; SILICON DIOXIDE; PENTAERYTHRITOL TETRAKIS(3-(3,5-DI-TERT-BUTYL-4-HYDROXYPHENYL)PROPIONATE); CHLOROXYLENOL; PHENOXYETHANOL; SORBIC ACID; FERRIC OXIDE YELLOW; CHROMIC OXIDE

ACTIVE INGREDIENT

ACTIVE INGREDIENTS: OCTINOXATE 3.40% [] TITANIUM DIOXIDE 1.00%

INACTIVE INGREDIENT

INACTIVE INGREDIENTS: WATER [] CYCLOPENTASILOXANE [] POLYMETHYL METHACRYLATE [] BUTYLENE GLYCOL [] PEG-10 DIMETHICONE [] TRIMETHYLSILOXYSILICATE [] DIMETHICONE [] MAGNESIUM SULFATE [] TOCOPHEROL [] TOCOPHERYL ACETATE [] SODIUM HYALURONATE [] LECITHIN [] HYDROGENATED LECITHIN [] ALGAE EXTRACT [] LAMINARIA SACCHARINA EXTRACT [] DIPROPYLENE GLYCOL [] XANTHAN GUM [] LAURETH-7 [] SORBITAN SESQUIOLEATE [] DIMETHICONE/PEG-10/15 CROSSPOLYMER [] DIMETHICONE/PEG-10 CROSSPOLYMER [] PEG/PPG-18/18 DIMETHICONE [] TRIETHOXYCAPRYLYLSILANE [] DIMETHICONE SILYLATE [] DIMETHICONE CROSSPOLYMER [] SILICA [] PENTAERYTHRITYL TETRA-DI-T-BUTYL HYDROXYHYDROCINNAMATE [] CHLOROXYLENOL [] PHENOXYETHANOL [] SORBIC ACID [] [+/- IRON OXIDES (CI 77491, CI 77492, CI 77499) [] TITANIUM DIOXIDE (CI 77891) [] CHROMIUM OXIDE GREENS (CI 77288)]

WARNINGS

WARNING: KEEP OUT OF EYES. IF IRRITATION PERSISTS STOP USE AN CONTACT A HEALTH CARE PRACTITIONER. KEEP OUT OF REACH OF CHILDREN. APPLY BEFORE SUN EXPOSURE

PACKAGE LABEL

PRINCIPAL DISPLAY PANEL:

MAC

MATCHMASTER FOUNDATION

SPF 15

1.2 FL. OZ. LIQ/35 ML

MAKEUP ART COSMETICS, DIST

TORONTO, ONTARIO, CANADA, M5V 1R7